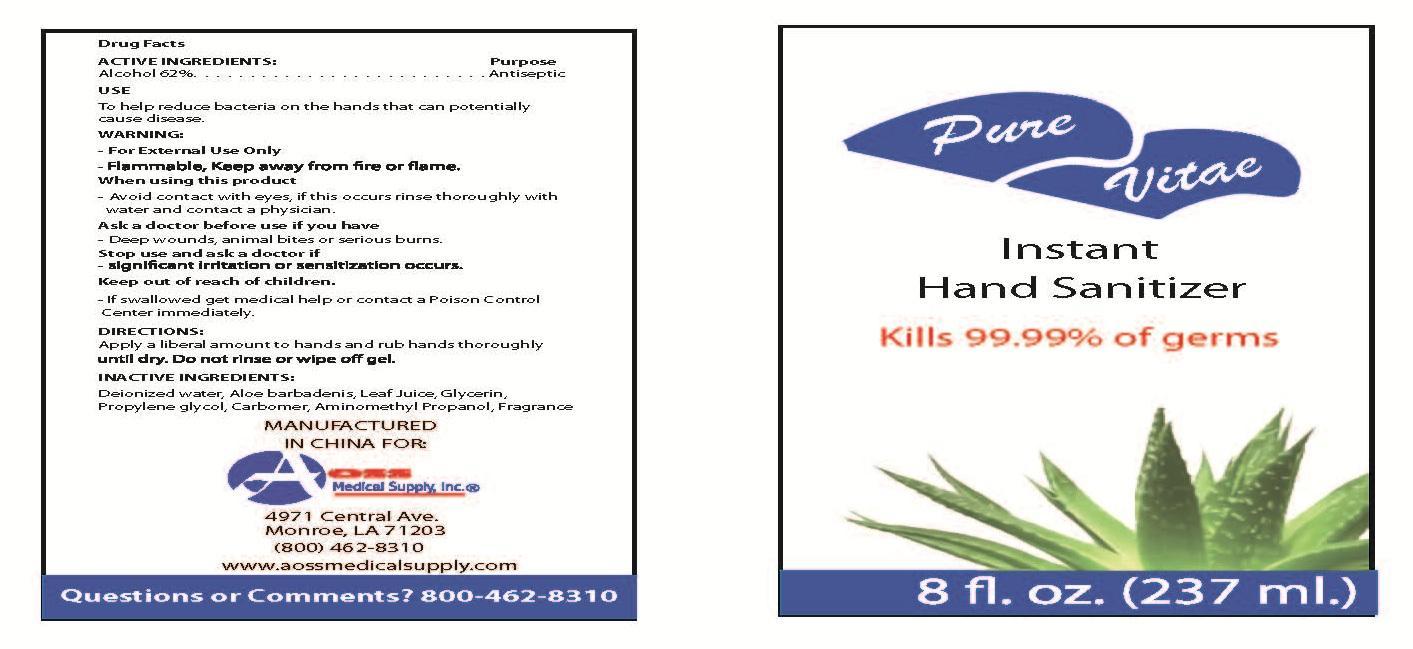 DRUG LABEL: Instant Hand Sanitizer
                
NDC: 53152-1008 | Form: GEL
Manufacturer: AOSS Medical Supply, Inc. 
Category: otc | Type: HUMAN OTC DRUG LABEL
Date: 20120828

ACTIVE INGREDIENTS: Alcohol 62 mL/100 mL
INACTIVE INGREDIENTS: WATER; ALOE; ALOE VERA LEAF; GLYCERIN; PROPYLENE GLYCOL; CARBOMER HOMOPOLYMER TYPE C (ALLYL PENTAERYTHRITOL CROSSLINKED); AMINOMETHYLPROPANOL

Active ingredients
Ethyl Alcohol 62%

Purpose
Antiseptic

Uses
To help reduce bacteria on the hands that can potentially cause disease.

Warning
For External Use Only.
Flammable, Keep away from fire or flame.

When using this product
Avoid contact with eyes, if this occurs rinse thoroughly with water and contact a physician.

Ask a doctor before use if you have
Deep wounds, animal bites or serious burns.

Stop use and ask a doctor if
significant irritation or sensitization occurs.

Keep out of reach of children.
If swallowed get medical help or contact a Poison Control
Center immediately.

DIRECTIONS:
Apply a liberal amount to hands and rub hands thoroughly until dry. Do not rinse or wipe off gel.

INACTIVE INGREDIENTS:
Deionized water, Aloe barbadenis, Leaf Juice, Glycerin,
Propylene glycol, Carbomer, Aminomethyl Propanol, Fragrance